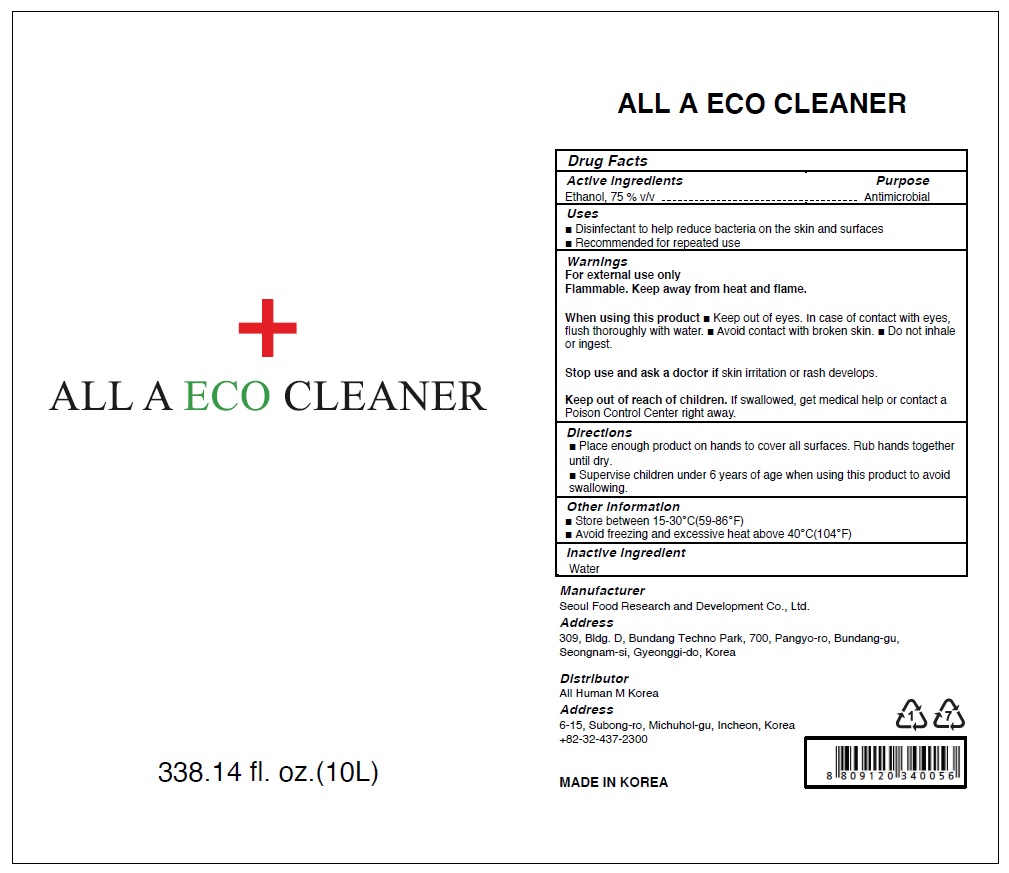 DRUG LABEL: ALL A ECO CLEANER
NDC: 81158-010 | Form: LIQUID
Manufacturer: All Human M Korea
Category: otc | Type: HUMAN OTC DRUG LABEL
Date: 20201123

ACTIVE INGREDIENTS: ALCOHOL 750 mL/1000 mL
INACTIVE INGREDIENTS: Water

ACTIVE INGREDIENT

Ethanol 75 % v/v

INACTIVE INGREDIENT

Water

PURPOSE

Antimicrobial

WARNINGS

For external use only
Flammable. Keep away from heat and flame.

When using this product ■ Keep out of eyes. In case of contact with eyes,
flush thoroughly with water. ■ Avoid contact with broken skin. ■ Do not inhale or ingest.

Stop use and ask a doctor if skin irritation or rash develops.

Keep out of reach of children. If swallowed, get medical help or contact a Poison Control Center right away.

Keep out of reach of children. If swallowed, get medical help or contact a Poison Control Center right away.

Uses

■ Disinfectant to help reduce bacteria on the skin and surfaces
■ Recommended for repeated use

Directions

■ Place enough product on hands to cover all surfaces. Rub hands together until dry.
■ Supervise children under 6 years of age when using this product to avoid swallowing.

Other information

■ Store between 15-30℃(59-86℉)
■ Avoid freezing and excessive heat above 40℃(104℉)